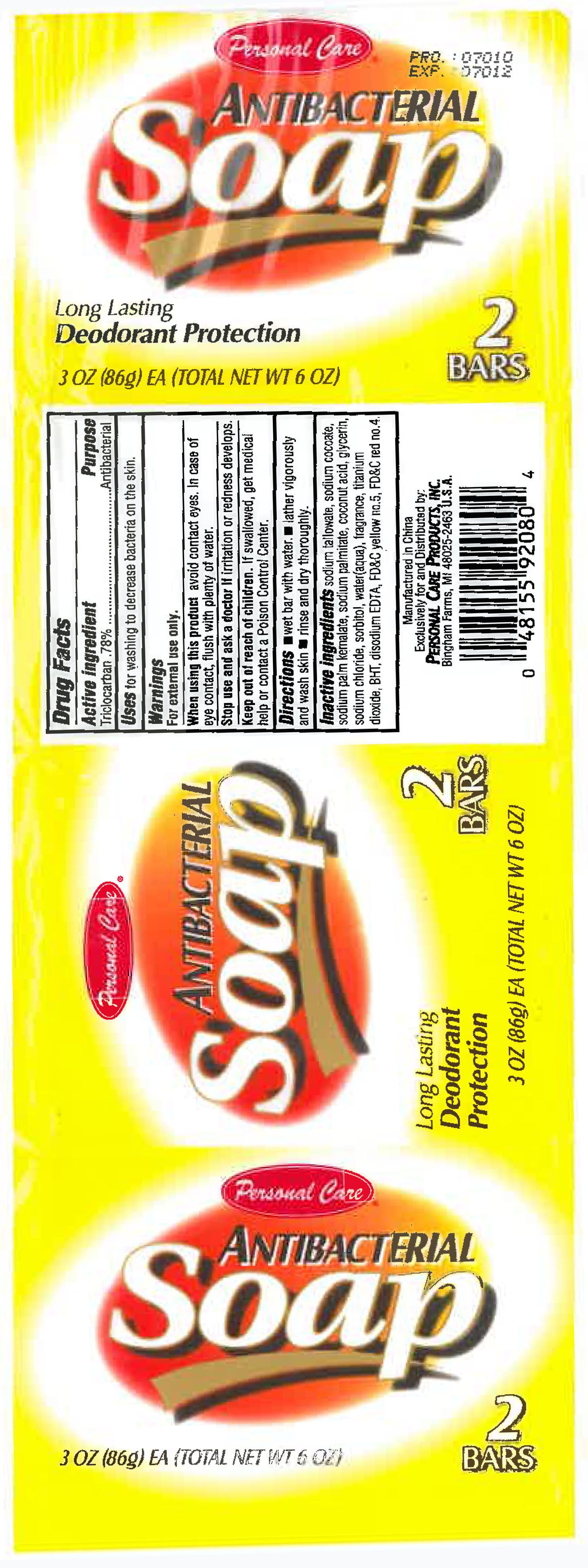 DRUG LABEL: Personal Care Antibacterial
                        
NDC: 29500-9208 | Form: SOAP
Manufacturer: Personal Care Products LLC
Category: otc | Type: HUMAN OTC DRUG LABEL
Date: 20120111

ACTIVE INGREDIENTS: TRICLOCARBAN .67 g/86 g
INACTIVE INGREDIENTS: SODIUM TALLOWATE, BEEF; SODIUM COCOATE; SODIUM PALM KERNELATE; SODIUM PALMITATE; COCONUT ACID; GLYCERIN; SODIUM CHLORIDE; SORBITOL; WATER; TITANIUM DIOXIDE; BUTYLATED HYDROXYTOLUENE; EDETATE DISODIUM; FD&C YELLOW NO. 5; FD&C RED NO. 4

Personal Care Antibacterial

Active ingredient Purpose

Triclocarban .78% Antibacterial

Stop use and ask a doctor if irritation or redness develops.

Keep out of reach of children. If swallowed, get medical help or contact a Poison Control Center.

Purpose Antibacterial

When using this product avoid contact eyes. In case of eye contact, flush with plenty of water.

Stop use and ask a doctor if irritation or redness develops.

Directions

- Wet bar with water
- lather vigorously and wash skin
- rinse and dry thoroughly

INDICATIONS AND USAGE

Uses for washing to decrease bacteria on the skin.

INACTIVE INGREDIENT

Inactive ingredients sodium tallowate, sodium cocoate, sodium palm kernalate, sodium palmitate, cocnut acid, glycerin, sodium chloride, sorbitol, water(aqua), fragrance, titanium dioxide, BHT, disodium EDTA,

warnings For external use only

PACKAGE LABEL

Personal Care

Antibacterial Soap

Long lasting Deodorant protection

2 bars

3 oz (86 g)ea (Total net wt 6 oz)